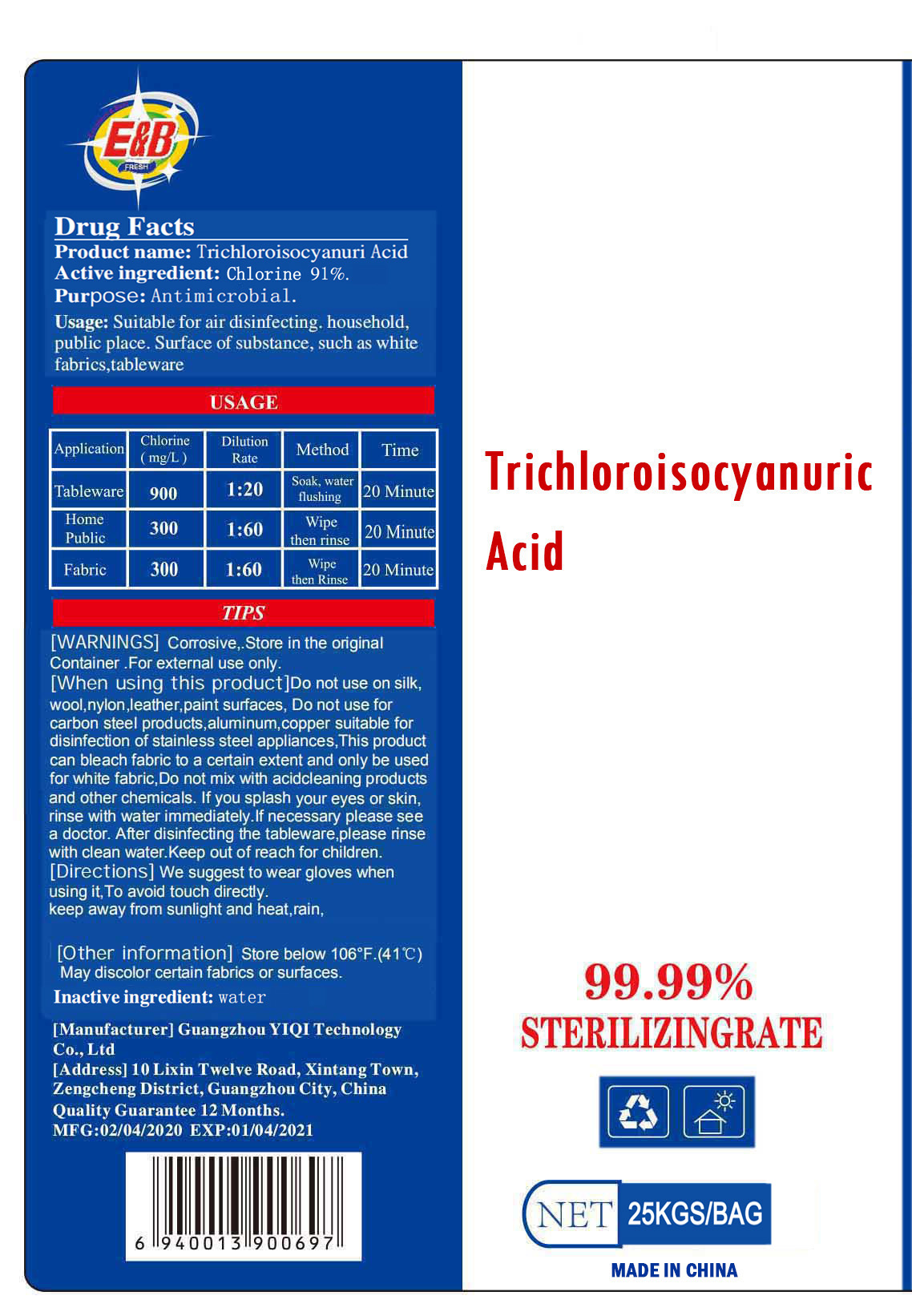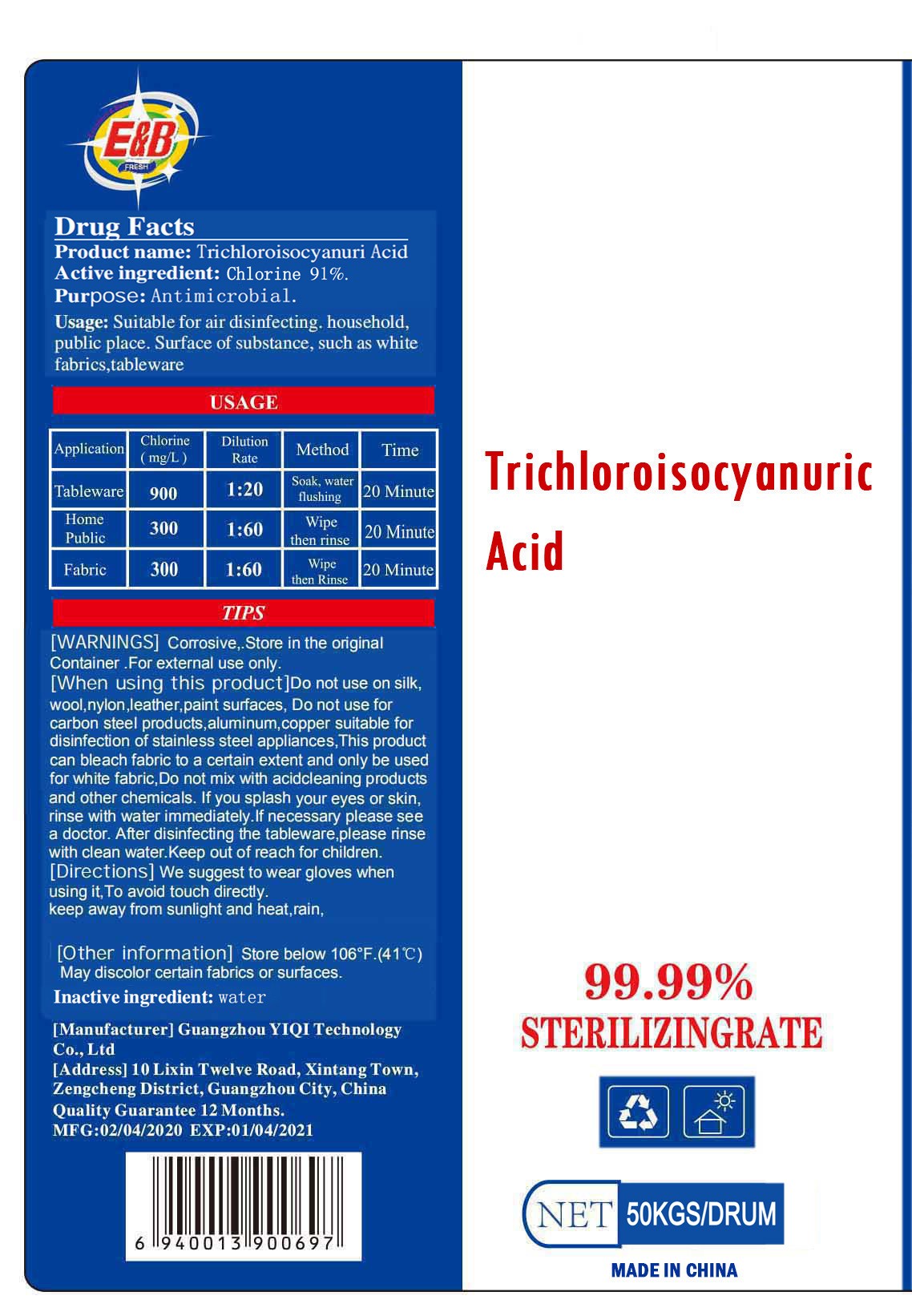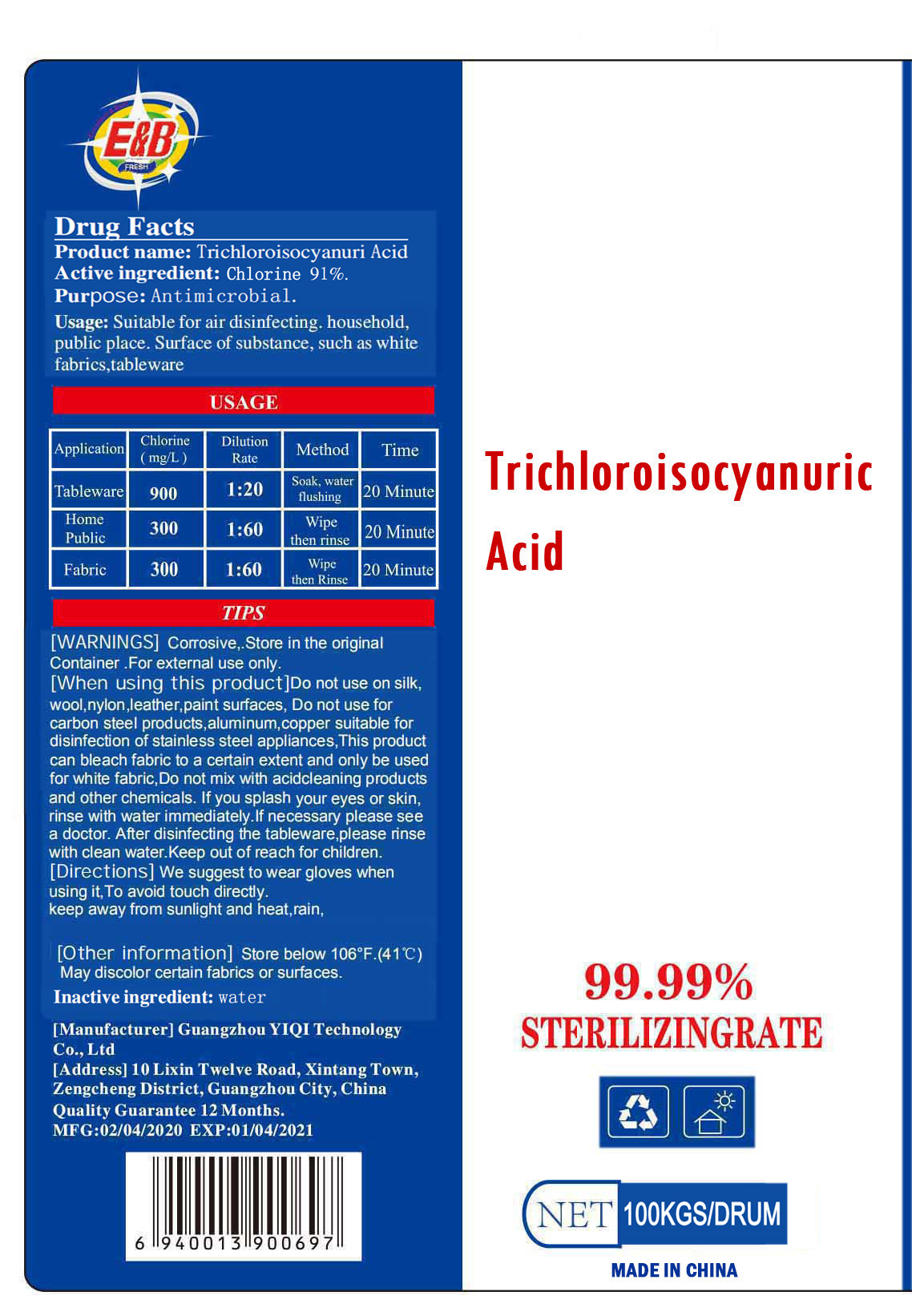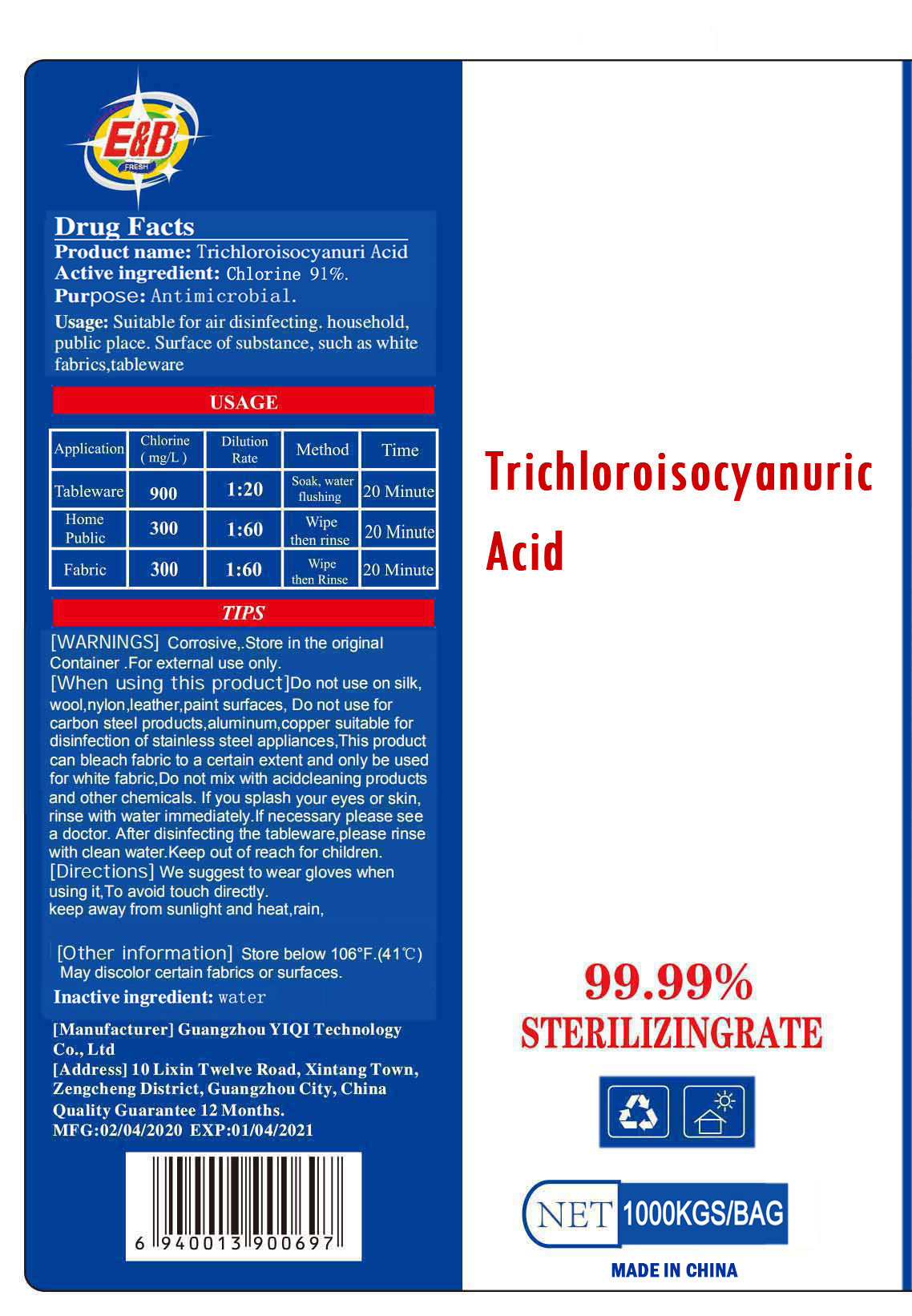 DRUG LABEL: Trichloroisocyanuric Acid
NDC: 78295-010 | Form: LIQUID
Manufacturer: GUANGZHOU YIQI TECHNOLOGY CO.,LTD
Category: otc | Type: HUMAN OTC DRUG LABEL
Date: 20201216

ACTIVE INGREDIENTS: CHLORINE 91 kg/100 kg
INACTIVE INGREDIENTS: WATER

78295-010
78295-009 replaced by 78295-010
Trichloroisocyanuric Acid

Active ingredient

Active ingredient: Chlorine 91%.

Purpose

Purpose: Antimicrobial.

WARNINGS

Corrosive， .Store in the orginal Container.For external use only.

INDICATIONS AND USAGE

Usage:Suitable for air disinfecting.household, public place.Surface of substance, such as white fabrics, tableware

Application | Chlorine(mg/L) | Dilution Rate | method | Time
Tableware | 900 | 1:20 | Soak, water flushing | 20 Minute
Home Public | 300 | 1:60 | Wipe then rinse | 20 Minute
Fabric | 300 | 1:60 | wipc then rinse | 20 Minute

DO NOT USE

/

When using this product

Do not use on sik，wool， nylon， leather， paint surfaces， Do not use for carbon steel products， aluminum， copper suitable for disinfection of stainless steel appliances， This product can bleach fabric to a certain extent and only be used for white fabric， Do not mix with acid cleaning products and other chemicals.If you splash your eyes or skin，rinse with water immediately.If necessary please see a doctor.After disinfecting the tableware， please rinse with clean water.Keep out of reach for children.

STOP USE

/

KEEP OUT OF REACH OF CHILDREN

/

Directions

We suggest to wear gloves when using it To avoid touch directly. keep away from sunlight and heat， rain，

Other information

Store below 106°F.(41C)
May discolor certain fabrics or surfaces.

Inactive ingredient

Inactive ingredient: water

Package Label - Principal Display Panel

78295-010-01 25KGS 1 BAG

78295-010-02 50KGS 1 DRUM

78295-010-03 100KGS 1 DRUM

78295-010-04 1000KGS 1 BAG